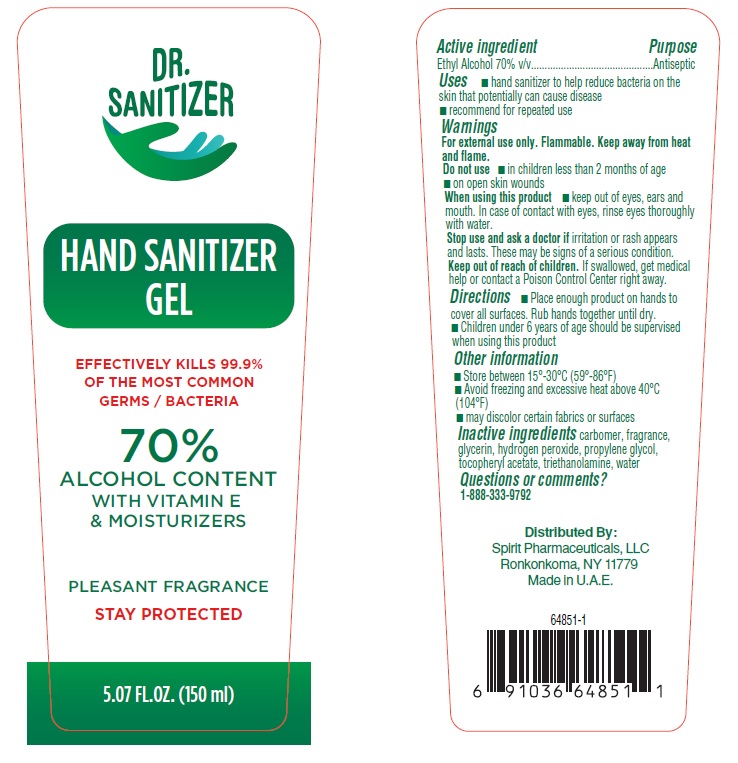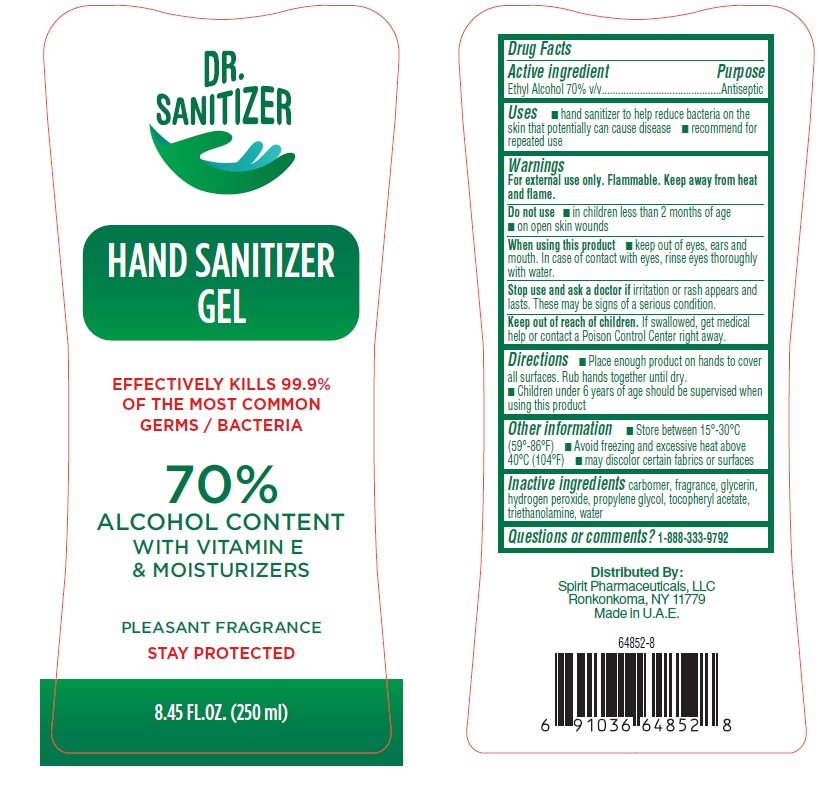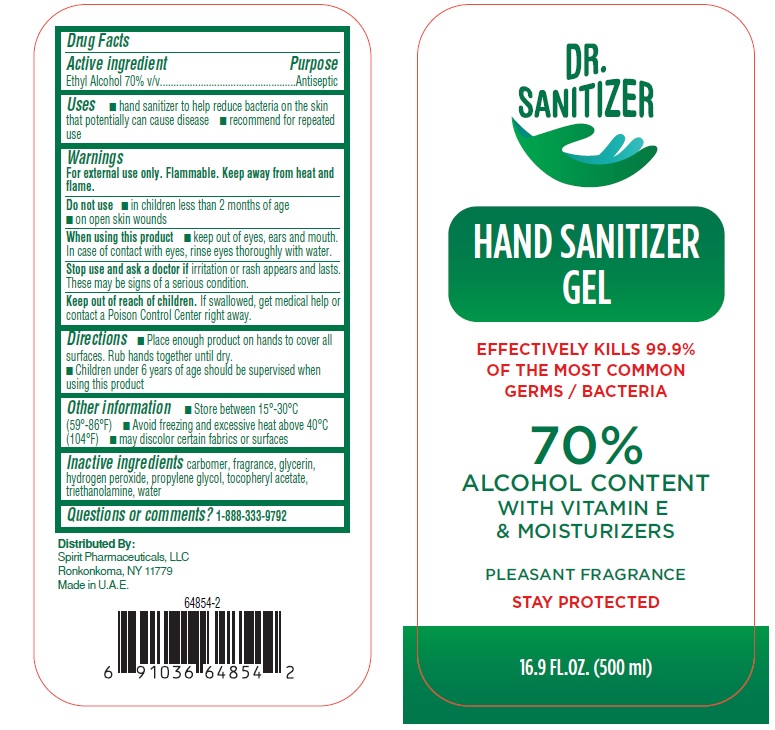 DRUG LABEL: Hand Sanitizer Gel
NDC: 68210-4081 | Form: GEL
Manufacturer: SPIRIT PHARMACEUTICALS LLC
Category: otc | Type: HUMAN OTC DRUG LABEL
Date: 20221205

ACTIVE INGREDIENTS: ALCOHOL 70 mL/100 mL
INACTIVE INGREDIENTS: CARBOMER HOMOPOLYMER, UNSPECIFIED TYPE; GLYCERIN; HYDROGEN PEROXIDE; PROPYLENE GLYCOL; .ALPHA.-TOCOPHEROL ACETATE; TROLAMINE

Dr. SANITIZER HAND SANITIZER gel

Active ingredient

Ethyl alcohol 70%

Purpose

Antiseptic

Uses

• hand sanitizer to help reduce bacteria on the skin that potentially can cause disease
• recommend for repeated use

Warnings

For external use only. Flammable. Keep away from heat and flame.
Do not use • in children less than 2 months of age
• on open skin wounds
___________________________________________________________________________
When using this product
• keep out of eyes, ears and mouth. In case of contact with eyes, rinse eyes thoroughly with water.
___________________________________________________________________________
Stop use and ask a doctor if irritation or rash appears and lasts. These may be signs of a serious condition.

Keep out of reach of children. If swallowed, get medical help or contact a Poison Control Center right away.

Directions

- Place enough product on hands to cover all surfaces. Rub hands together until dry.
- Children under 6 years of age should be supervised when using this product

Other Information

• Store between 15°-30°C (59°86°F)
• Avoid freezing and excessive heat above 40°C (104°F)
• may discolor certain fabrics or surfaces

Inactive ingredients

carbomer, fragrance, glycerin, hydrogen peroxide, propylene glycol, tocopheryl acetate, triethanolamine, water

Questions or comments?

1-888-333-9792

PRINCIPAL DISPLAY PANEL

Dr. SANITIZER

HAND-SANITIZER GEL

EFFECTIVELY KILLS 99.9% OF THE

MOST COMMON GERMS/ BACTERIA

70%

ALCOHOL CONTENT

WITH

VITAMIN E & MOISTURIZERS

PLEASANT FRAGRANCE

STAY PROTECTED

150 ml / 250 ml / 500 ml